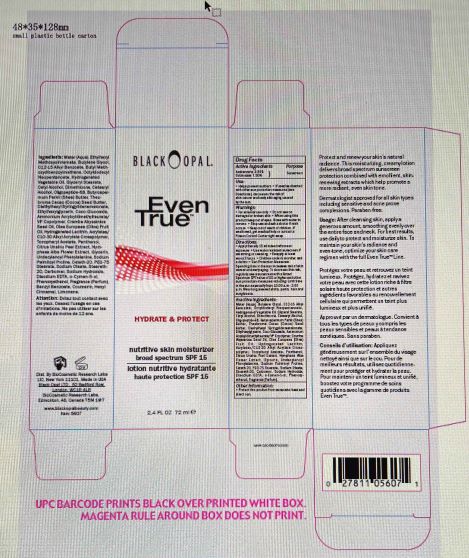 DRUG LABEL: EVEN TRUE NUTRITIVE SKIN MOISTURIZER SPF 15
NDC: 59735-550 | Form: CREAM
Manufacturer: MANA PRODUCTS, INC.
Category: otc | Type: HUMAN OTC DRUG LABEL
Date: 20240103

ACTIVE INGREDIENTS: AVOBENZONE 3 g/100 g; OCTINOXATE 7.5 g/100 g
INACTIVE INGREDIENTS: BUTYLENE GLYCOL; ALKYL (C12-15) BENZOATE; OCTYLDODECYL NEOPENTANOATE; CETYL ALCOHOL; ORANGE PEEL; GLYCERYL STEARATE SE; CETOSTEARYL ALCOHOL; PEG-75 STEARATE; DIMETHICONE 200; COCOA BUTTER; SOYBEAN OIL; SODIUM HYDROXIDE; PANTHENOL; OCTYLDODECANOL; ETHYLHEXYLGLYCERIN; CARBOMER INTERPOLYMER TYPE A (ALLYL SUCROSE CROSSLINKED); CRAMBE HISPANICA SUBSP. ABYSSINICA SEED OIL; MEDIUM-CHAIN TRIGLYCERIDES; SODIUM PALMITOYL PROLINE; HYDROGENATED COTTONSEED OIL; WATER; OLIVE OIL; O-CYMEN-5-OL; HYALURONATE SODIUM; UNDECYLENOYL PHENYLALANINE; PHENOXYETHANOL; DIETHYLHEXYL SYRINGYLIDENEMALONATE; SHEA BUTTER; AMMONIUM ACRYLOYLDIMETHYLTAURATE/VP COPOLYMER; COCO GLUCOSIDE; CARBOMER 940; CETETH-20; STEARETH-20; .ALPHA.-TOCOPHEROL ACETATE; NYMPHAEA ALBA FLOWER; HYDROGENATED SOYBEAN LECITHIN; PALMITOYL HEXAPEPTIDE-12; EDETATE DISODIUM; FRAGRANCE 13576; DIPROPYLENE GLYCOL; GLYCERIN

EVEN TRUE NUTRITIVE SKIN MOISTURIZER SPF 15

ACTIVE INGREDIENTS

Avobenzone 3.000000
Octinoxate 7.5

PURPOSE

SUNSCREEN

USES

Helps prevent sunburn. If used as directed with other sun protection measures (see directions), decreases the risk of skin cancer and early skin aging caused by the sun.

WARNINGS

For external use only. Do not use on damaged or broken skin. When using this product keep out of eyes. Rinse with water to remove.

DIRECTIONS

- Apply liberally 15 minutes before sun exposure.
- Use a water-resistant sunscreen if swimming or sweating.
- Reapply at least every 2 hours,
- Children under 6 months: ask a doctor.

Sun Protection Measures: Spending time in the sun increases risk of skin cancer and early aging. To decrease this risk, regularly use a sunscreen with a Broad-Spectrum SPF value of 15 or higher and other sun protection measures including: limit time in the sun especially from 10:00 a.m. - 2:00 p.m.

- Wear long sleeved shirts, pants, hats and sunglasses.

INACTIVE INGREDIENTS

Aqua/Water/Eau ,Butylene Glycol,C12-15 Alkyl Benzoate,Octyldodecyl Neopentanoate ,Cetyl Alcohol,Hydrogenated Vegetable Oil ,
Dimethicone ,Glyceryl Stearate ,Cetearyl Alcohol ,Theobroma Cacao (Cocoa) Seed Butter,Butyrospermum Parkii (Shea) Butter ,
Diethylhexyl Syringylidenemalonate,PEG-75 Stearate,Ammonium Acryloyldimethyltaurate/VP Copolymer,Coco-Glucoside ,
Carbomer,Ceteth-20 ,Steareth-20,Tocopheryl Acetate ,Sodium Hydroxide ,Acrylates/C10-30 Alkyl Acrylate Crosspolymer ,
Crambe Abyssinica Seed Oil ,Panthenol,Octyldodecanol,Caprylic/Capric Triglyceride,Undecylenoyl Phenylalanine,
Olea Europaea (Olive) Fruit Oil ,Citrus Unshiu Peel Extract,Dipropylene Glycol0.000000 ,Sodium Palmitoyl Proline ,Nymphaea Alba Flower Extract ,Glycerin ,Sodium Hyaluronate ,Glycine Soja (Soybean) Oil,Oligopeptide-68 ,Hydrogenated Lecithin,Sodium Oleate ,

o-Cymen-5-ol ,Disodium EDTA ,Ethylhexylglycerin ,Phenoxyethanol ,Fragrance .

Stop use and ask a doctor if rash occurs.

RECENT MAJOR CHANGES

dosage & admin update

Keep out of reach of children. If product is swallowed, get medical help or contact a Poison Control Center right away.